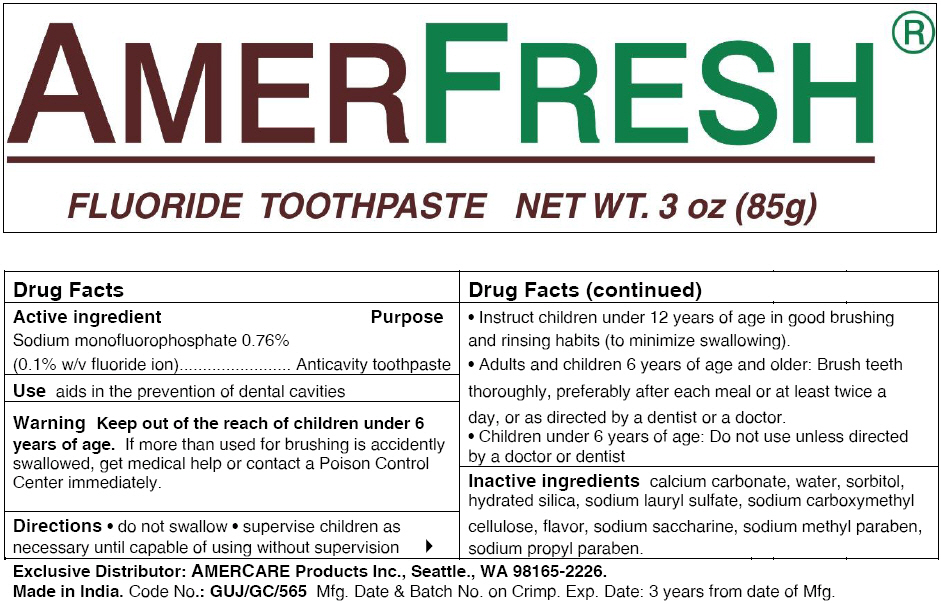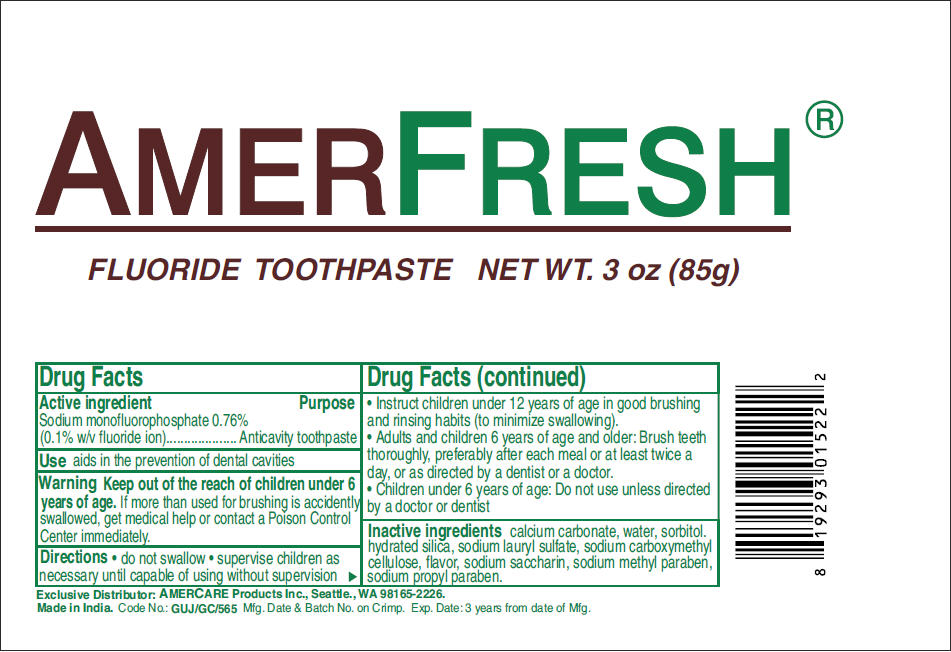 DRUG LABEL: AmerFresh
NDC: 51460-1112 | Form: PASTE, DENTIFRICE
Manufacturer: Amercare Products, Inc.
Category: otc | Type: HUMAN OTC DRUG LABEL
Date: 20150115

ACTIVE INGREDIENTS: Sodium Monofluorophosphate 1 mg/1 g
INACTIVE INGREDIENTS: Calcium Carbonate; Water; Sorbitol; Hydrated Silica; Sodium Lauryl Sulfate; Carboxymethylcellulose Sodium; Saccharin Sodium; Methylparaben Sodium; Propylparaben Sodium

AmerFresh®
Fluoride Toothpaste

Drug Facts

Active ingredient

Sodium monofluorophosphate 0.76% (0.1% w/v fluoride ion)

Purpose

Anticavity toothpaste

Use

aids in the prevention of dental cavities

Warning

KEEP OUT OF REACH OF CHILDREN

Keep out of the reach of children under 6 years of age. If more than used for brushing is accidently swallowed, get medical help or contact a Poison Control Center immediately.

Directions

- do not swallow
- supervise children as necessary until capable of using without supervision
- Instruct children under 12 years of age in good brushing and rinsing habits (to minimize swallowing).
- Adults and children 6 years of age and older: Brush teeth thoroughly, preferably after each meal or at least twice a day, or as directed by a dentist or a doctor.
- Children under 6 years of age: Do not use unless directed by a doctor or dentist

Inactive ingredients

calcium carbonate, water, sorbitol, hydrated silica, sodium lauryl sulfate, sodium carboxymethyl cellulose, flavor, sodium saccharine, sodium methyl paraben, sodium propyl paraben.

Exclusive Distributor: AMERCARE Products Inc., Seattle., WA 98165-2226.

PRINCIPAL DISPLAY PANEL - 85 g Tube Label - NDC 51460-1112

AMERFRESH®

FLUORIDE TOOTHPASTE NET WT. 3 oz (85g)

PRINCIPAL DISPLAY PANEL - 85 g Tube Label - NDC 51460-1114

AMERFRESH®

FLUORIDE TOOTHPASTE NET WT. 3 oz (85g)